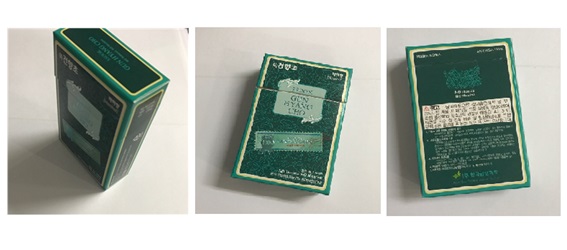 DRUG LABEL: SSOOK GUN HYANG CHO(hazelnut)
NDC: 70378-004 | Form: INHALANT
Manufacturer: KOREA STOP Smoking science CO., LTD.
Category: otc | Type: HUMAN OTC DRUG LABEL
Date: 20170419

ACTIVE INGREDIENTS: WORMWOOD 1 g/1 g
INACTIVE INGREDIENTS: HAZELNUT, UNSPECIFIED

Drug Facts

ACTIVE INGREDIENT

Wormwood

INACTIVE INGREDIENT

Hazelnut flavor

PURPOSE

Stop-smoking aids

keep out of reach of the children

INDICATIONS AND USAGE

Smoke 10 a day

WARNINGS

- Do not take if you have an allergy to medicinal herbs.
- Do not take if you are pregnant or breast feeding

DOSAGE AND ADMINISTRATION

for external use only